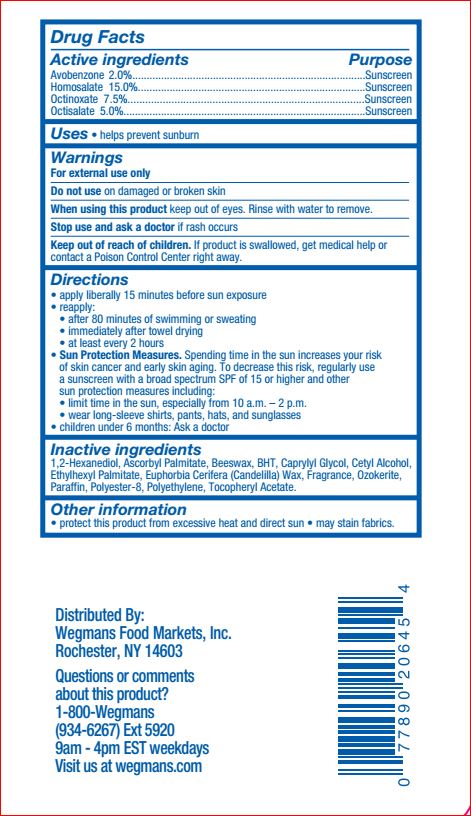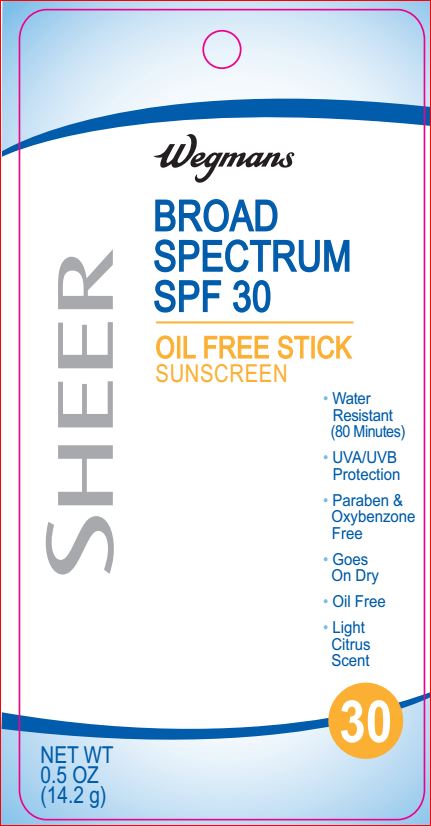 DRUG LABEL: Sheer Sunscreen SPF 30

NDC: 47124-447 | Form: STICK
Manufacturer: Wegman
Category: otc | Type: HUMAN OTC DRUG LABEL
Date: 20180109

ACTIVE INGREDIENTS: AVOBENZONE 2 g/100 g; HOMOSALATE 15 g/100 g; OCTINOXATE 7.5 g/100 g; OCTISALATE 5 g/100 g
INACTIVE INGREDIENTS: 1,2-HEXANEDIOL; ASCORBYL PALMITATE; YELLOW WAX; BUTYLATED HYDROXYTOLUENE; CAPRYLYL GLYCOL; CETYL ALCOHOL; ETHYLHEXYL PALMITATE; CANDELILLA WAX; CERESIN; PARAFFIN; .ALPHA.-TOCOPHEROL ACETATE; HIGH DENSITY POLYETHYLENE

Active ingredients Purpose

Avobenzone 2%...........................Sunscreen
Homosalate 15%..........................Sunscreen
Octinoxate 7.50%.................... ....Sunscreen
Octisalate 5.00%..........................Sunscreen

INDICATIONS AND USAGE

Uses • helps prevent sunburn

INDICATIONS AND USAGE

Uses • helps prevent sunburn

Warnings

For external use only
Do not use on damaged or broken skin
When using this product keep out of eyes. Rinse with water to remove.
Stop use and ask a doctor if rash occurs
Keep out of reach of children. If product is swallowed, get medical help or contact a Poison Control Center right away.

Directions

• apply liberally 15 minutes before sun exposure
• reapply: • after 80 minutes of swimming or sweating
• immediately after towel drying • at least every 2 hours
• Sun Protection Measures. Spending time in the sun
increases your risk of skin cancer and early skin aging.
To decrease this risk, regularly use a sunscreen with a
broad spectrum SPF of 15 or higher and other sun
protection measures including:
• limit time in the sun, especially from 10 a.m. – 2 p.m.
• wear long-sleeve shirts, pants, hats, and sunglasses
• children under 6 months: Ask a doctor

Inactive ingredients

1,2-Hexanediol
Ascorbyl Palmitate
Beeswax
BHT
Caprylyl Glycol
Cetyl Alcohol
Ethylhexyl Palmitate
Euphorbia Cerifera (Candelilla) Wax
Fragrance
Ozokerite
Paraffin
Polyester-8
Polyethylene
Tocopheryl Acetate